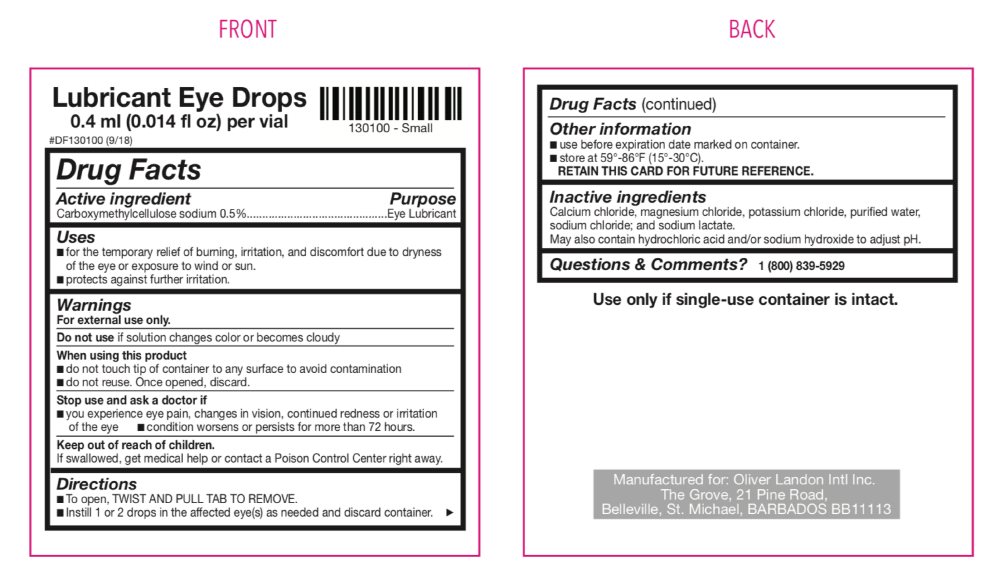 DRUG LABEL: Lubricant Eye Drops
NDC: 59276-905 | Form: SOLUTION/ DROPS
Manufacturer: Oliver Landon Intl Inc.
Category: otc | Type: HUMAN OTC DRUG LABEL
Date: 20201124

ACTIVE INGREDIENTS: CARBOXYMETHYLCELLULOSE SODIUM 5 mg/1 mL
INACTIVE INGREDIENTS: CALCIUM CHLORIDE; MAGNESIUM CHLORIDE; POTASSIUM CHLORIDE; WATER; SODIUM CHLORIDE; SODIUM LACTATE; HYDROCHLORIC ACID; SODIUM HYDROXIDE

Lubricant Eye Drops

Drug Facts

Active ingredient

Carboxymethylcellulose sodium 0.5%

Purpose

Eye Lubricant

Uses

- for the temporary relief of burning, irritation and discomfort due to dryness of the eye or exposure to wind or sun.
- protects against further irritation.

Warnings

For external use only

Do not use if solution changes color or becomes cloudy

When using this product

- do not touch tip of container to any surface to avoid contamination.
- do not reuse. Once opened, discard.

Stop use and ask a doctor if

- you experience eye pain, changes in vision, continued redness or irritation of the eye
- condition worsens or persists for more than 72 hours.

Keep out of reach of children. If swallowed, get medical help or contact a Poison Control Center right away.

Directions

- To open, TWIST AND PULL TAB TO REMOVE.
- Instill 1 or 2 drops in the affected eye(s) as needed and discard container.

*If used for post-operative dryness and discomfort, follow your eye doctor’s instructions.

Other information

- use before expiration date marked on container.
- store at 59°-86°F (15°-33°C)

RETAIN THIS CARD FOR FUTURE REFERENCE.

Use only if single-use container is intact.

INACTIVE INGREDIENT

Inactive ingredients Calcium chloride, magnesium chloride, potassium chloride, purified water, sodium chloride and sodium lactate.

May also contain hydrochloric acid and/or sodium hydroxide to adjust pH.

Questions & Comments? 1 (800) 839-5929

Manufactured for: Oliver Landon Intl. Inc.

The Grove, 21 Pine Road

Belleville, St. Michael, BARBADOS BB11113

PACKAGE LABEL

Lubricant Eye Drops
0.4 ml (0.014 fl oz) per vial